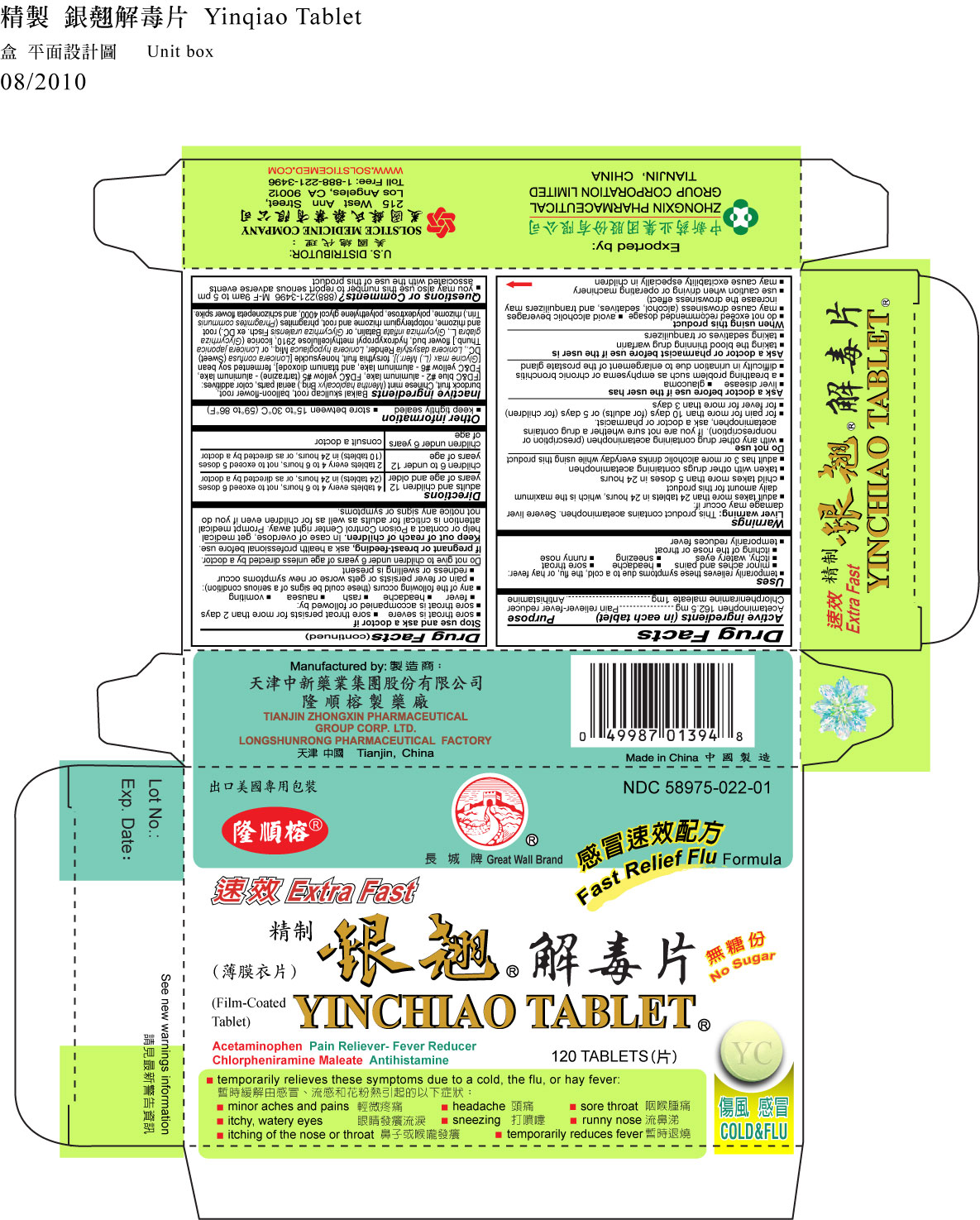 DRUG LABEL: YINCHIAO
NDC: 58975-022 | Form: TABLET, FILM COATED
Manufacturer: TIANJIN ZHONGXIN PHARMACEUTICAL GROUP CORP LTD LONGSHUNRONG PHARMACEUTICAL FACTORY
Category: otc | Type: HUMAN OTC DRUG LABEL
Date: 20110216

ACTIVE INGREDIENTS: ACETAMINOPHEN 162.5 mg/1 1; CHLORPHENIRAMINE MALEATE 1 mg/1 1
INACTIVE INGREDIENTS: SCUTELLARIA BAICALENSIS ROOT; PLATYCODON GRANDIFLORUM LEAF; ARCTIUM LAPPA FRUIT; MINT; FD&C BLUE NO. 2; FD&C YELLOW NO. 5; FD&C YELLOW NO. 6; TITANIUM DIOXIDE; SOYBEAN; FORSYTHIA SUSPENSA FRUIT; LONICERA JAPONICA FLOWER; HYPROMELLOSE 2910 (15000 MPA.S); GLYCYRRHIZA URALENSIS; NOTOPTERYGIUM INCISUM ROOT; PHRAGMITES AUSTRALIS ROOT; POLYDEXTROSE; POLYETHYLENE GLYCOL 4000; SCHIZONEPETA TENUFOLIA SPIKE

DRUG FACTS

Active ingredient (in each tablet)
Acetaminophen 162.5 mg
Chlorpheniramine maleate 1 mg

Purpose
Pain reliever-fever reducer
Antihistamine

Uses
temporarily relieves these symptoms due to a cold, the flu, or hay fever:
minor aches and pains headache
sore throat
sneezing
runny nose
itchy, watery eyes
itching of the nose or throat
temporarily reduces fever

Warnings
Liver warning: This product contains acetaminophen. Severe liver damage may occur if:
adult takes more than 24 tablets in 24 hours, which is the maximum daily amount for this product
child takes more than 5 doses in 24 hours
taken with other drugs containing acetaminophen
adult has 3 or more alcoholic drinks everyday while using this product
Do not give to children under 6 years of age unless directed by a doctor.

Do not use
with any other drug containing acetaminophen (prescription or nonprescription). If you are not sure whether a drug contains acetaminophen, ask a doctor or pharmacist.
for pain for more than 10 days (for adults) or 5 days (for children)
for fever for more than 3 days

Ask a doctor before use if the user has
liver disease
glaucoma
a breathing problem such as emphysema or chronic bronchitis
difficulty in urination due to enlargement of the prostate gland

Ask a doctor or pharmacist before use if the user is
taking the blood thinning drug warfarin
taking sedatives or tranquilizers

When using this product
do not exceed recommended dosage
avoid alcoholic beverages
may cause drowsiness (alcohol, sedatives, and tranquilizers may increase the drowsiness effect)
use caution when driving or operating machinery
may cause excitability especially in children

Stop use and ask a doctor if
sore throat is severe
sore throat persists for more than 2 days
sore throat is accompanied or followed by:
fever
headache
rash
nausea
vomiting
any of the following occurs (these could be signs of a serious condition):
pain or fever persists or gets worse or new symptoms occur
redness or swelling is present

PREGNANCY OR BREAST FEEDING

If pregnant or breast-feeding, ask a health professional before use.

Keep out of reach of children. In case of overdose, get medical help or contact a Poison Control
Center right away. Prompt medical attention is critical for adults as well as for children even if you do
not notice any signs or symptoms.

Directions
adults and children 12 years of age and older: 4 tablets every 4 to 6 hours, not to exceed 6 doses (24 tablets) in 24 hours, or as directed by a doctor
children 6 to under 12 years of age: 2 tablets every 4 to 6 hours, not to exceed 5 doses (10 tablets) in 24 hours, or as directed by a doctor
children under 6 years: consult a doctor of age

Other information
keep tightly sealed
store between 15º to 30º C (59º to 86º F)

Questions or Comments? (888) 221-3496 M-F 9 am to 5 pm
you may also use this number to report serious adverse events associated with the use of this product

Inactive ingredients
Scutellaria baicalensis root, platycodon grandiflorum leaf, arctium lappa fruit, mint, FDC blue no. 2, FDC yellow no.5, FDC yellow no.6, titanium dioxide, soybean, forsythia suspensa fruit, lonicera japonica flower, hypromellose 2910 (15000 mpa.s), glycyrrhiza uralensis, notopterygium incisum root, phragmites australis root, polydextrose, polyethylene glycol 4000, schizonepeta tenufolia spike

PACKAGE LABEL

YINCHIAO, NDC58975-022-01, Acetaminophen - Pain Reliever-Fever Reducer, Chlorpheniramine Maleate - Antihistamine, See new warnings information, 120 Tablets